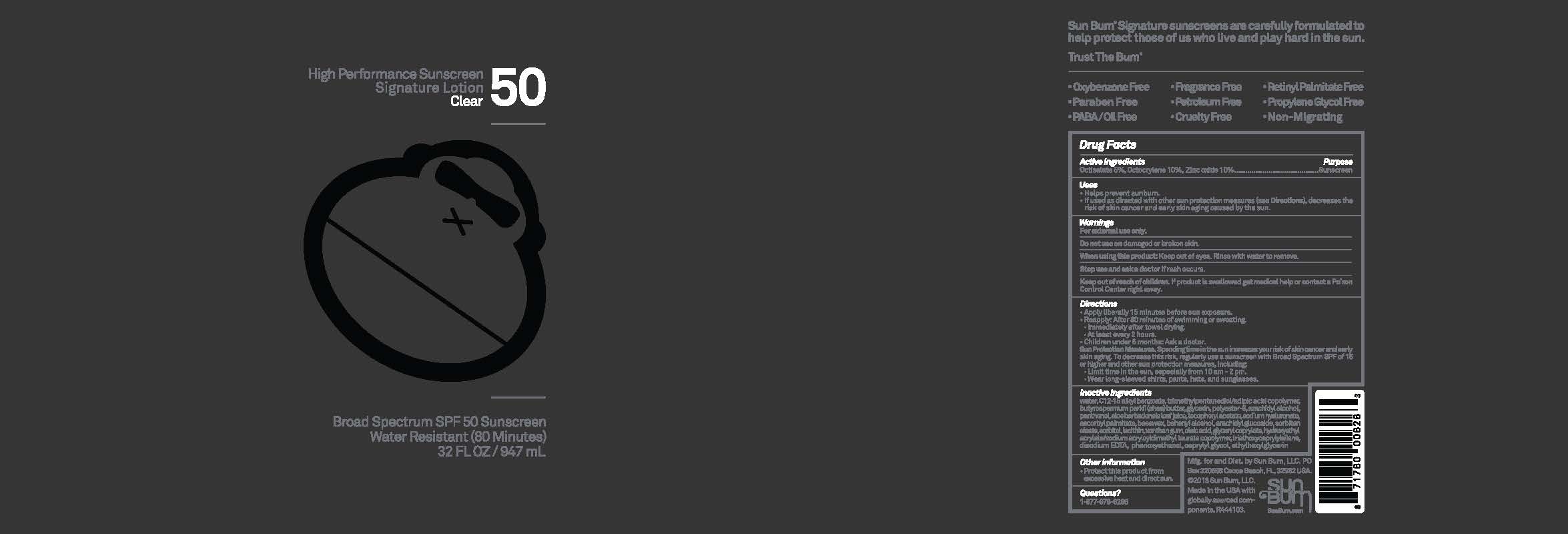 DRUG LABEL: Sun Bum High Performance Sunscreen Signature Clear 50 New
NDC: 69039-708 | Form: LOTION
Manufacturer: Sun Bum, LLC
Category: otc | Type: HUMAN OTC DRUG LABEL
Date: 20250812

ACTIVE INGREDIENTS: OCTISALATE 50 mg/1 mL; ZINC OXIDE 100 mg/1 mL; OCTOCRYLENE 100 mg/1 mL
INACTIVE INGREDIENTS: C12-15 ALKYL BENZOATE; XANTHAN GUM; GLYCERYL CAPRYLATE; ARACHIDYL ALCOHOL; PANTHENOL; ARACHIDYL GLUCOSIDE; SODIUM HYALURONATE; ALOE BARBADENSIS LEAF JUICE; ASCORBYL PALMITATE; SORBITAN OLEATE; OLEIC ACID; HYDROXYETHYL ACRYLATE/SODIUM ACRYLOYLDIMETHYL TAURATE COPOLYMER (45000 MPA.S AT 1%); TRIETHOXYCAPRYLYLSILANE; EDETATE DISODIUM; PHENOXYETHANOL; ETHYLHEXYLGLYCERIN; BUTYROSPERMUM PARKII (SHEA) BUTTER; TRIMETHYLPENTANEDIOL/ADIPIC ACID/GLYCERIN CROSSPOLYMER (25000 MPA.S); BEESWAX; BEHENYL ALCOHOL; CAPRYLYL GLYCOL; GLYCERIN; SORBITOL; WATER; POLYESTER-8 (1400 MW, CYANODIPHENYLPROPENOYL CAPPED); .ALPHA.-TOCOPHEROL ACETATE; LECITHIN, SUNFLOWER

Sun Bum High Performance Sunscreen Signature Clear 50

Active Ingredients

Octocrylene 10%, Octisalate 5%, Zinc Oxide 10%

Purpose

Sunscreen

Uses

• helps prevent sunburn • if used as directed with other sun protection measures, (see Directions) decreases the risk of skin cancer and early skin aging caused by the sun

Warnings

For external use only

Do not use on damaged or broken skin

When using this product keep out of eyes. Rinse with water to remove.

Stop use and ask a doctor if rash occurs

Keep out of reach of children. If swallowed, get medical help or contact a Poison Control Center immediately.

Warnings

Keep Out Of Reach Of Children

Directions

• shake well before use

• apply liberally 15 minutes before sun exposure

• reapply: • after 80 minutes of swimming or sweating • immediately after towel drying • at least every 2 hours

• children under 6 months of age: ask a doctor

• Sun Protection Measures. Spending time in the sun increases your risk of skin cancer and early skin aging. To decrease this risk, regularly use a sunscreen with a Broad Spectrum SPF value of 15 or higher and other sun protection measures including:

• limit time in the sun, especially from 10 a.m.- 2 p.m.

• wear long-sleeved shirts, pants, hats and sunglasses

Directions

• shake well before use

• apply liberally 15 minutes before sun exposure

Other Information

protect this product from excessive heat and direct sun

Inactive Ingredients

water, C12-15 alkyl benzoate, trimethylpentanediol/adipic acid copolymer, butyrospermum parkii (shea) butter, glycerin, polyester-8, arachidyl alcohol, panthenol, aloe barbadensis leaf juice, tocopheryl acetate, sodium hyaluronate, ascorbyl palmitate, beeswax, behenyl alcohol, arachidyl glucoside, sorbitan oleate, sorbitol, lecithin, xanthan gum, oleic acid, glyceryl caprylate, hydroxyethyl acrylate/sodium acryloyldimethyl taurate copolymer, Triethoxycaprylylsilane, disodium EDTA, phenoxyethanol, caprylyl glycol, ethylhexylglycerin

Questions?

1-877-978-6286